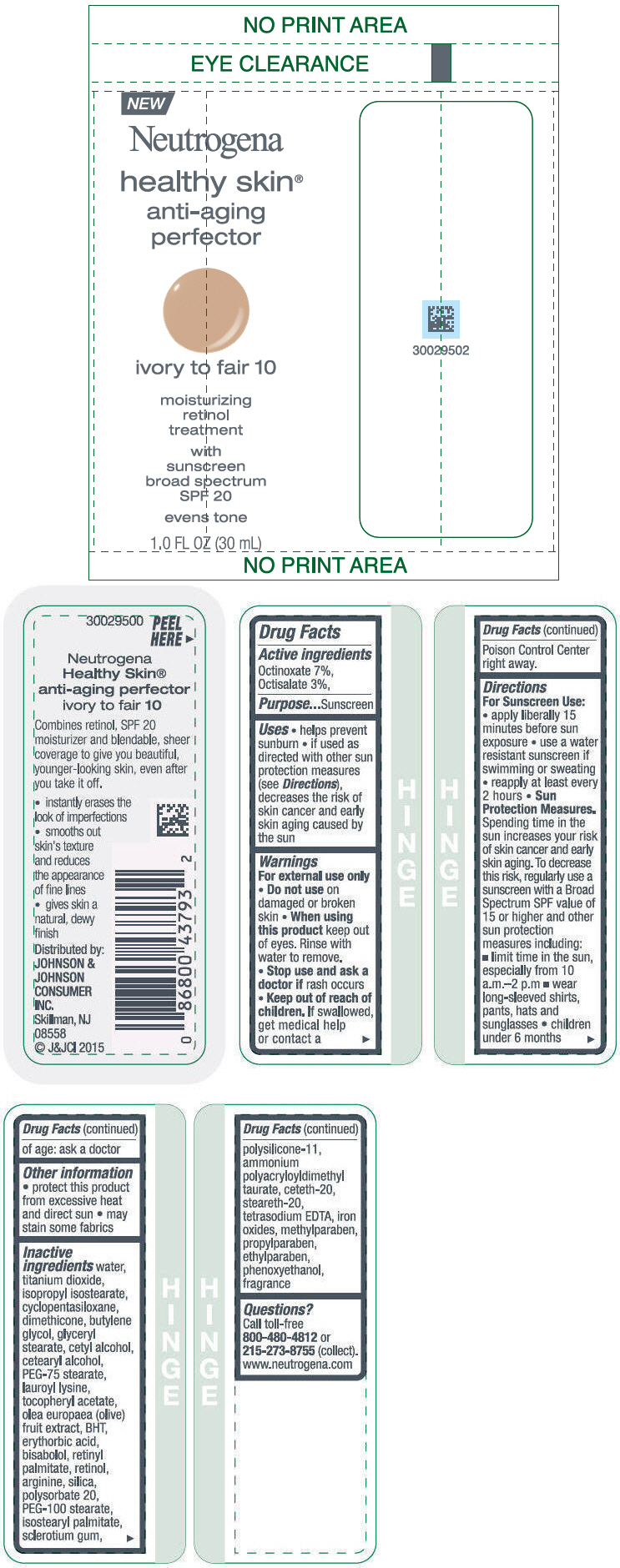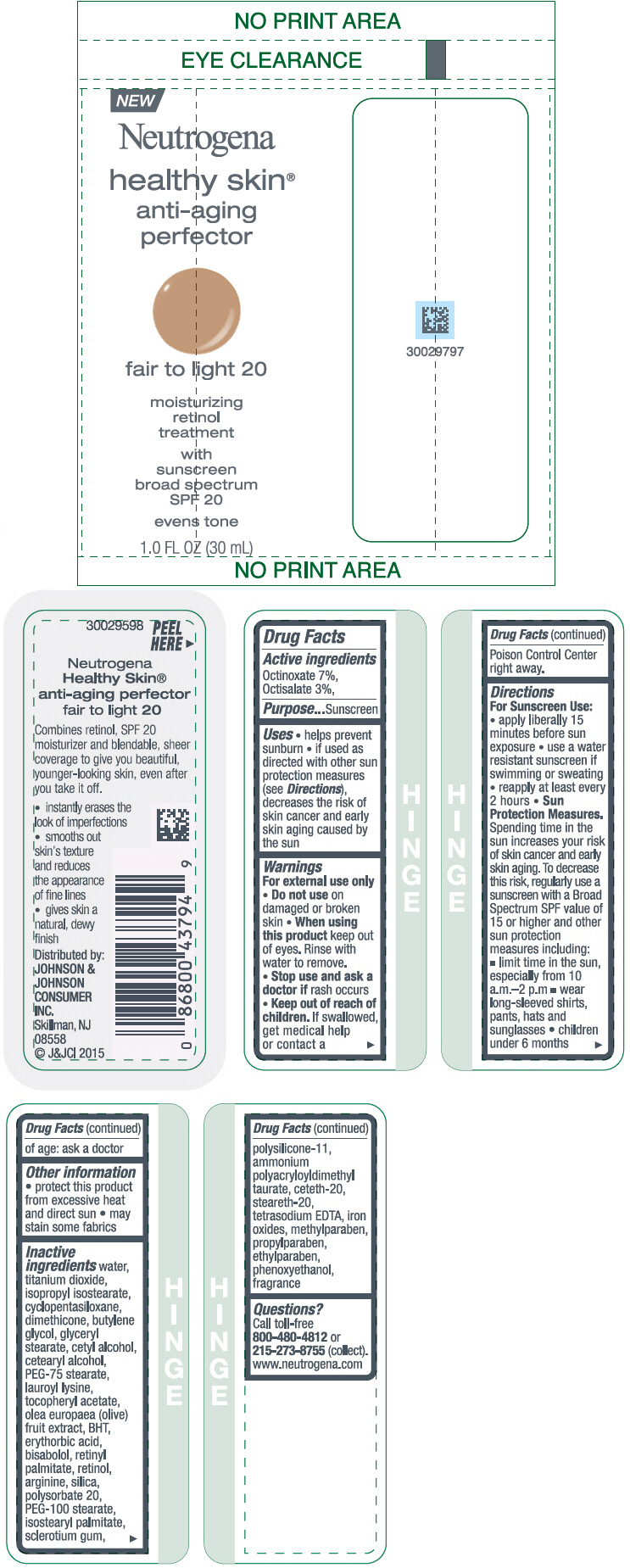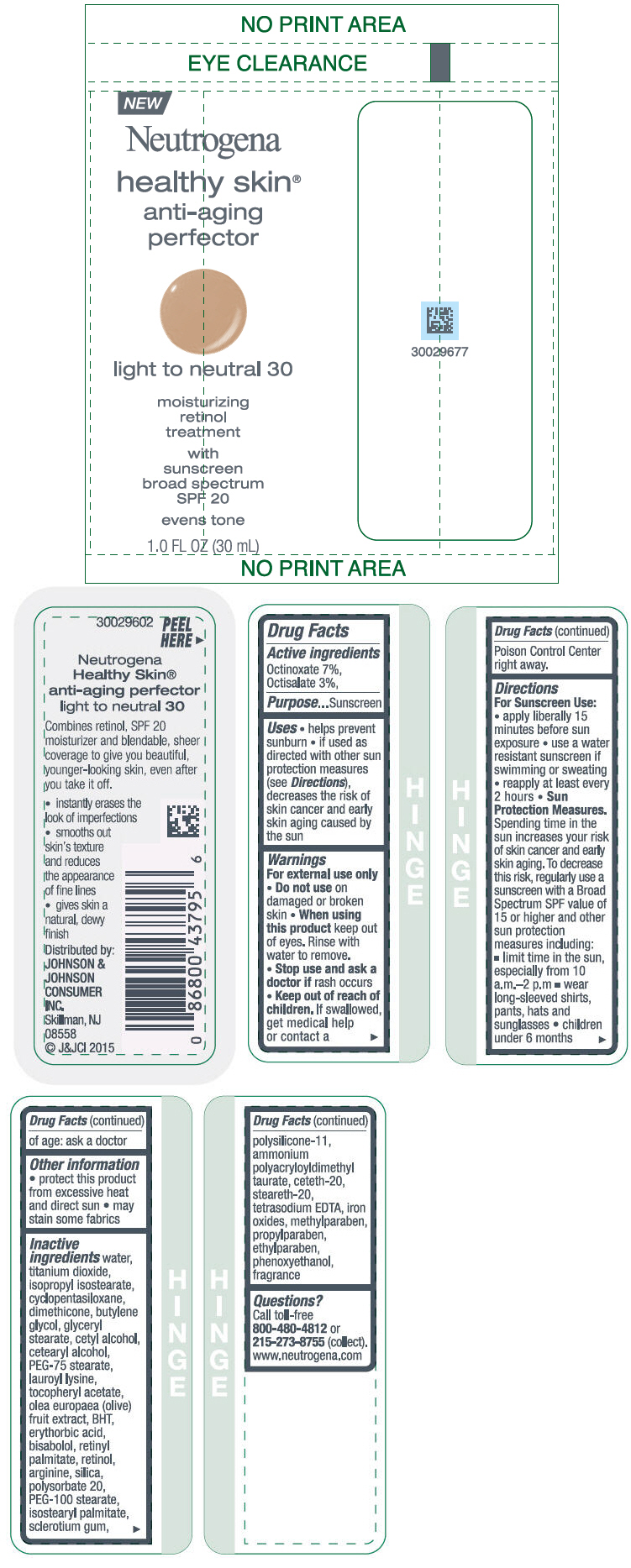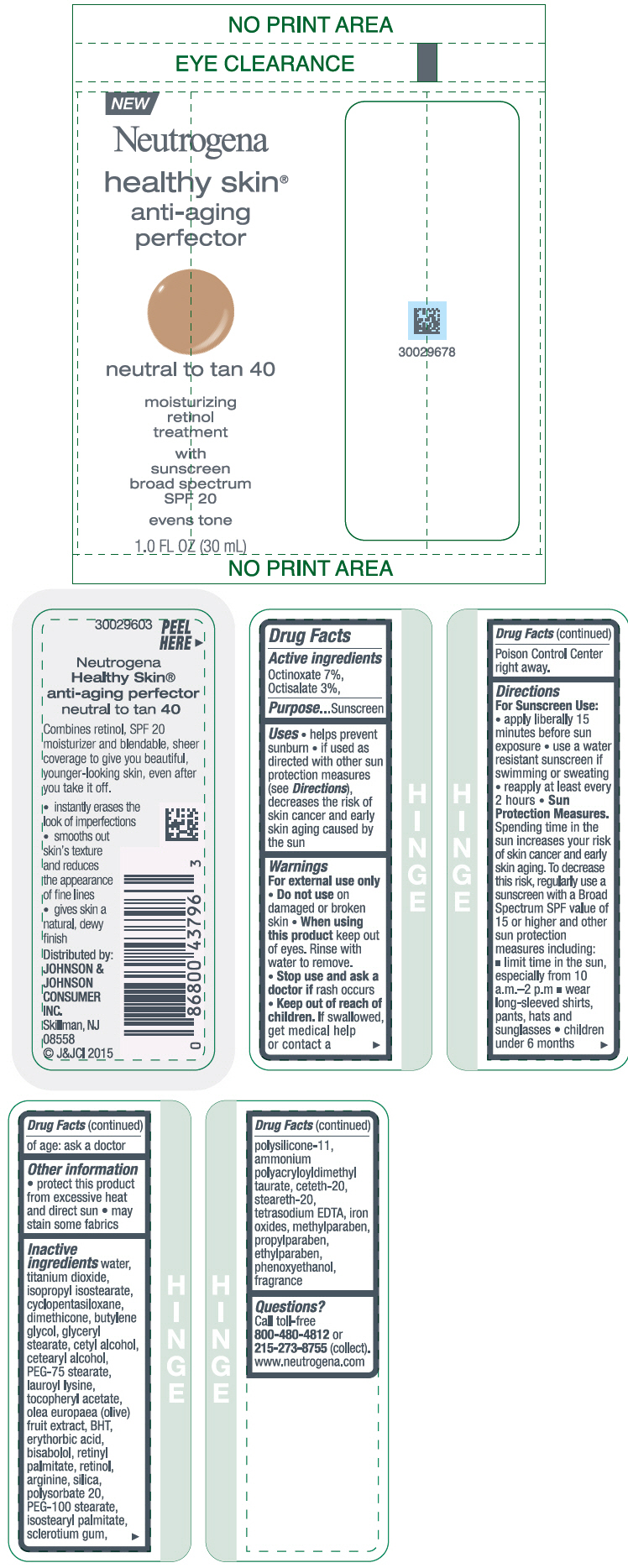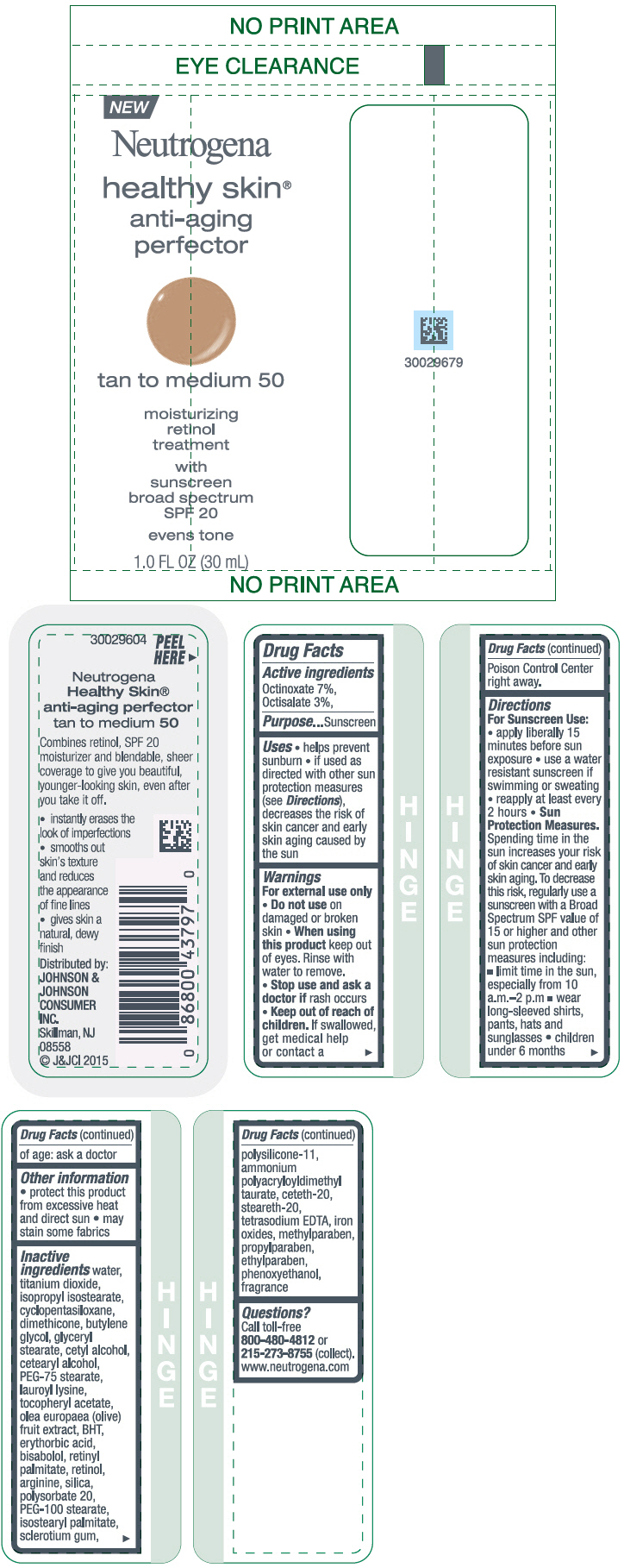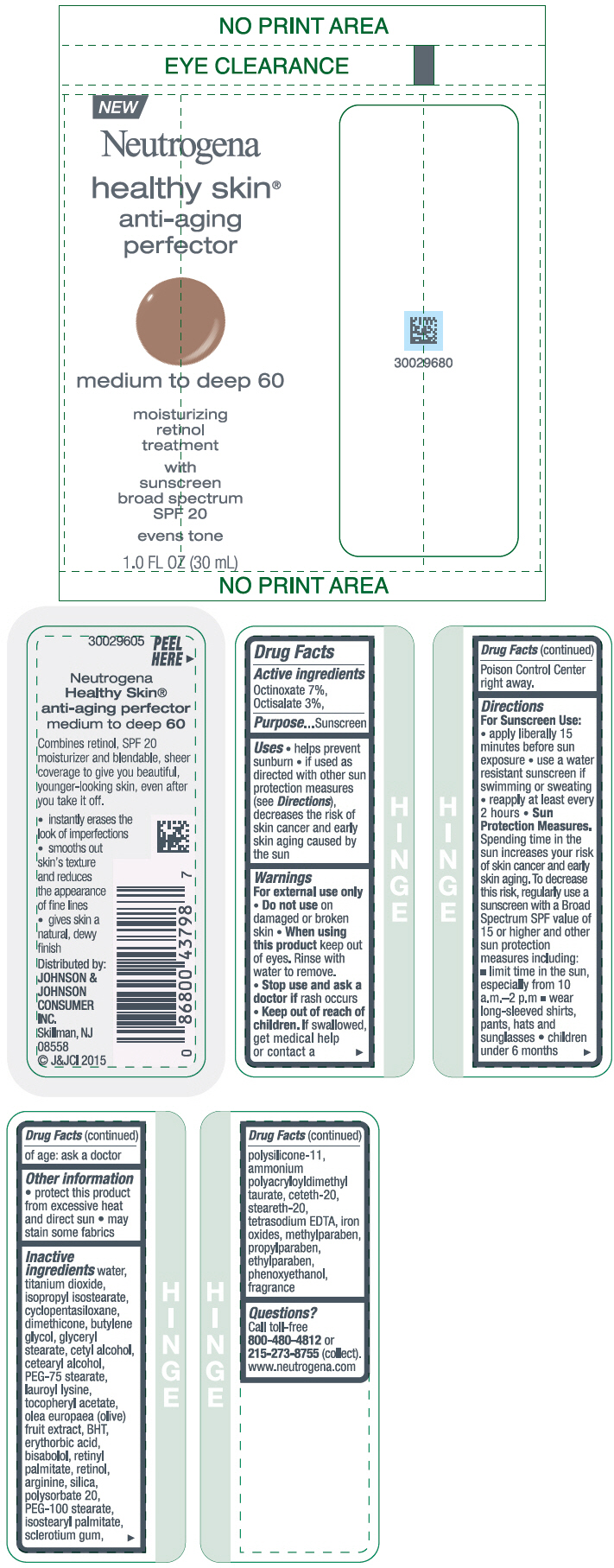 DRUG LABEL: Neutrogena Healthy Skin Anti-Aging Perfector Sunscreen Broad Spectrum SPF 20
NDC: 69968-0076 | Form: LOTION
Manufacturer: Kenvue Brands LLC
Category: otc | Type: HUMAN OTC DRUG LABEL
Date: 20241111

ACTIVE INGREDIENTS: OCTINOXATE 70 mg/1 mL; OCTISALATE 30 mg/1 mL
INACTIVE INGREDIENTS: WATER; TITANIUM DIOXIDE; ISOPROPYL ISOSTEARATE; CYCLOMETHICONE 5; DIMETHICONE; BUTYLENE GLYCOL; GLYCERYL MONOSTEARATE; CETYL ALCOHOL; CETOSTEARYL ALCOHOL; PEG-75 STEARATE; LAUROYL LYSINE; .ALPHA.-TOCOPHEROL ACETATE; BLACK OLIVE; BUTYLATED HYDROXYTOLUENE; ERYTHORBIC ACID; LEVOMENOL; VITAMIN A PALMITATE; RETINOL; ARGININE; SILICON DIOXIDE; POLYSORBATE 20; PEG-100 STEARATE; ISOSTEARYL PALMITATE; BETASIZOFIRAN; DIMETHICONE/VINYL DIMETHICONE CROSSPOLYMER (SOFT PARTICLE); CETETH-20; STEARETH-20; EDETATE SODIUM; FERRIC OXIDE RED; METHYLPARABEN; PROPYLPARABEN; ETHYLPARABEN; PHENOXYETHANOL

Neutrogena Healthy Skin Anti-Aging Perfector Sunscreen Broad Spectrum SPF20

Drug Facts

Active ingredients

Octinoxate 7%
Octisalate 3%

Purpose

Sunscreen

Uses

- helps prevent sunburn
- if used as directed with other sun protection measures (see Directions), decreases the risk of skin cancer and early skin aging caused by the sun

Warnings

For external use only

Do not use on damaged or broken skin

When using this product keep out of eyes. Rinse with water to remove.

Stop use and ask a doctor if rash occurs

Keep out of reach of children. If swallowed, get medical help or contact a Poison Control Center right away

Directions

- apply liberally 15 minutes before sun exposure
- use a water resistant sunscreen if swimming or sweating
- reapply at least every 2 hours.
- Sun Protection Measures. Spending time in the sun increases your risk of skin cancer and early skin aging. To decrease this risk, regularly use a sunscreen with a Broad Spectrum SPF value of 15 or higher and other sun protection measures including:
  - limit time in the sun, especially from 10 a.m. – 2 p.m.
  - wear long-sleeved shirts, pants, hats, and sunglasses
- children under 6 months of age: Ask a doctor

Other Information

- protect this product from excessive heat and direct sun
- may stain some fabrics

Inactive Ingredients

Water, Titanium Dioxide, Isopropyl Isostearate, Cyclopentasiloxane, Dimethicone, Butylene Glycol, Glyceryl Stearate, Cetyl Alcohol, Cetearyl Alcohol, PEG-75 Stearate, Lauroyl Lysine, Tocopheryl Acetate, Olea Europaea (Olive) Fruit Extract, BHT, Erythorbic Acid, Bisabolol, Retinyl Palmitate, Retinol, Arginine, Slica, Polysorbate 20, PEG-100 Stearate, Isostearyl Palmitate, Sclerotium Gum, Polysilicone-11, Ammonium Polyacryloyldimethyl Taurate, Ceteth-20, Steareth-20, Tetrasodium EDTA, Iron Oxides, Methylparaben, Propylparaben, Ethylparaben, Phenoxyethanol, Fragrance

Questions?

Call toll-free 800-480-4812 or 215-273-8755 (collect). www.neutrogena.com

Distributed by:
JOHNSON &
JOHNSON
CONSUMER
INC.
Skillman, NJ
08558

PRINCIPAL DISPLAY PANEL - 30 mL Bottle Label - ivory to fair 10

NEW
Neutrogena
healthy skin®
anti-aging
perfector

ivory to fair 10

moisturizing
retinol
treatment
with
sunscreen
broad spectrum
SPF 20

evens tone

1.0 FL OZ (30 mL)

PRINCIPAL DISPLAY PANEL - 30 mL Bottle Label - fair to light 20

NEW
Neutrogena
healthy skin®
anti-aging
perfector

fair to light 20

moisturizing
retinol
treatment
with
sunscreen
broad spectrum
SPF 20

evens tone

1.0 FL OZ (30 mL

PRINCIPAL DISPLAY PANEL - 30 mL Bottle Label - light to neutral 30

NEW
Neutrogena
healthy skin®
anti-aging
perfector

light to neutral 30

moisturizing
retinol
treatment
with
sunscreen
broad spectrum
SPF 20

evens tone

1.0 FL OZ (30 mL)

PRINCIPAL DISPLAY PANEL - 30 mL Bottle Label - neutral to tan 40

NEW
Neutrogena
healthy skin®
anti-aging
perfector

neutral to tan 40

moisturizing
retinol
treatment
with
sunscreen
broad spectrum
SPF 20

evens tone

1.0 FL OZ (30 mL)

PRINCIPAL DISPLAY PANEL - 30 mL Bottle Label - tan to medium 50

NEW
Neutrogena
healthy skin®
anti-aging
perfector

tan to medium 50

moisturizing
retinol
treatment
with
sunscreen
broad spectrum
SPF 20

evens tone

1.0 FL OZ (30 mL)

PRINCIPAL DISPLAY PANEL - 30 mL Bottle Label - medium to deep 60

NEW
Neutrogena
healthy skin®
anti-aging
perfector

medium to deep 60

moisturizing
retinol
treatment
with
sunscreen
broad spectrum
SPF 20

evens tone

1.0 FL OZ (30 mL)